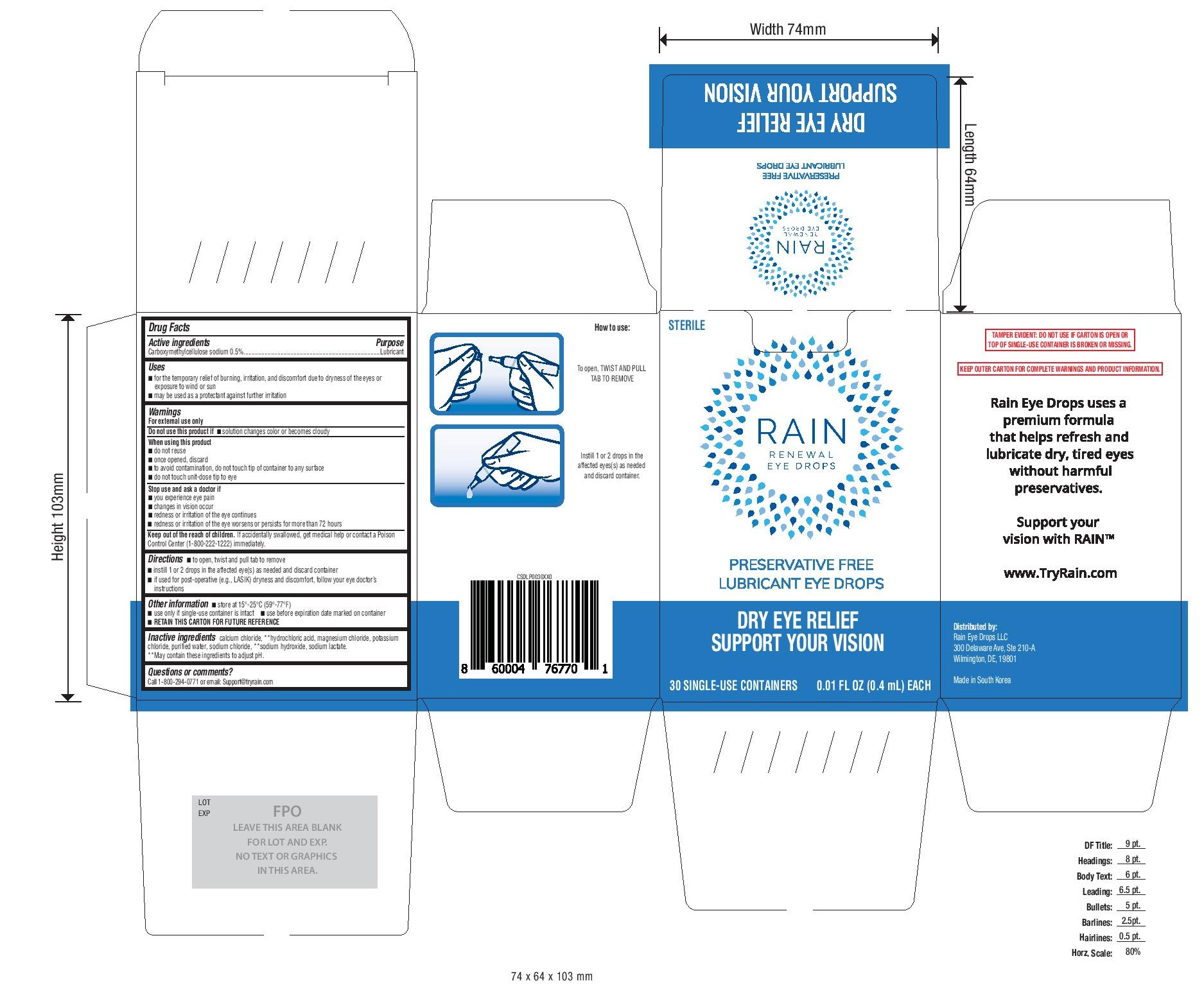 DRUG LABEL: Rain Renewal Eye Drops
NDC: 79662-001 | Form: SOLUTION/ DROPS
Manufacturer: Rain Eye Drops, LLC
Category: otc | Type: HUMAN OTC DRUG LABEL
Date: 20241229

ACTIVE INGREDIENTS: CARBOXYMETHYLCELLULOSE SODIUM, UNSPECIFIED FORM 0.5 g/100 mL
INACTIVE INGREDIENTS: MAGNESIUM CHLORIDE; HYDROCHLORIC ACID; SODIUM HYDROXIDE; CALCIUM CHLORIDE; WATER; POTASSIUM CHLORIDE; SODIUM LACTATE; SODIUM CHLORIDE

Rain Renewal Eye Drops Dry Eye Relief - 30ct (PLD)

Active ingredients

Carboxymethylcellulose sodium 0.5%

Purpose

Carboxymethylcellulose sodium.............Lubricant

Uses

- for the temporary relief of burning, irritation, and discomfort due to dryness of the eye or exposure to wind or sun
- may be used as a protectant against further irritation

Warnings

For external use only.

- Do not use if solution changes color or becomes cloudy.

When using the product

- do not reuse
- once opened, discard
- to avoid contamination do not touch tip of container to any surface
- do not touch unit-dose tip to eye.

Do not use this product if

solution changes color or becomes cloudy

When using this product

- do not reuse
- once opened, discard
- to avoid contamination do not touch tip of container to any surface
- do not touch unit-dose tip to eye

Stop use and ask a doctor if

- you experience eye pain
- changes in vision occur
- redness or irritation of the eye continues
- redness or irritation of the eye worsens or persists for more than 72 hours

Keep out of reach of children.

If accidentally swallowed, get medical help or contact a Poison Control Center (1-800-222-1222) immediately.

Directions

- To open, twist and pull tab to remove
- Instill 1 or 2 drops in the affected eye(s) as needed and discard container
- If used for post-operative (e.g., LASIK) dryness and discomfort, follow your eye doctor’s instructions.

Other information

- Store at 15°-25°C (59°-77°F)
- Use only if single-use container is intact
- Use before expiration date marked on container

RETAIN THIS CARTON FOR FUTURE REFERENCE

Inactive ingredients

calcium chloride, **hydrochloric acid, magnesium chloride, potassium chloride, purified water, sodium chloride, **sodium hydroxide, sodium lactate.

**May contain these ingredients to adjust pH.

Questions or comments?

Call 1-800-294-0771 or email: Support@tryrain.com